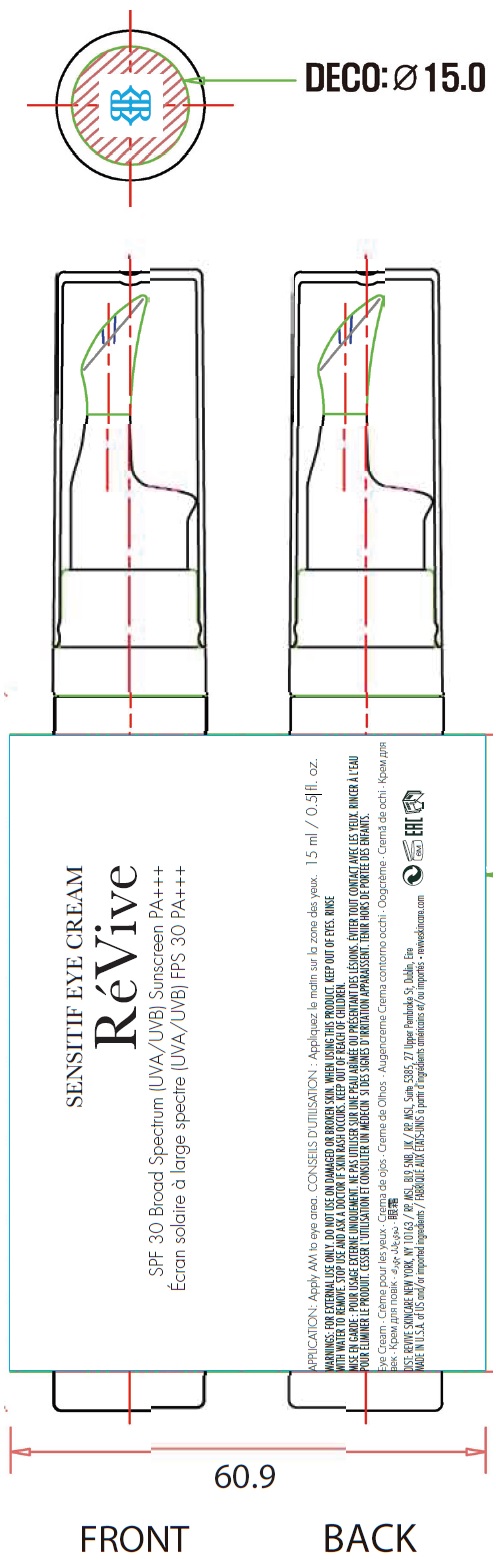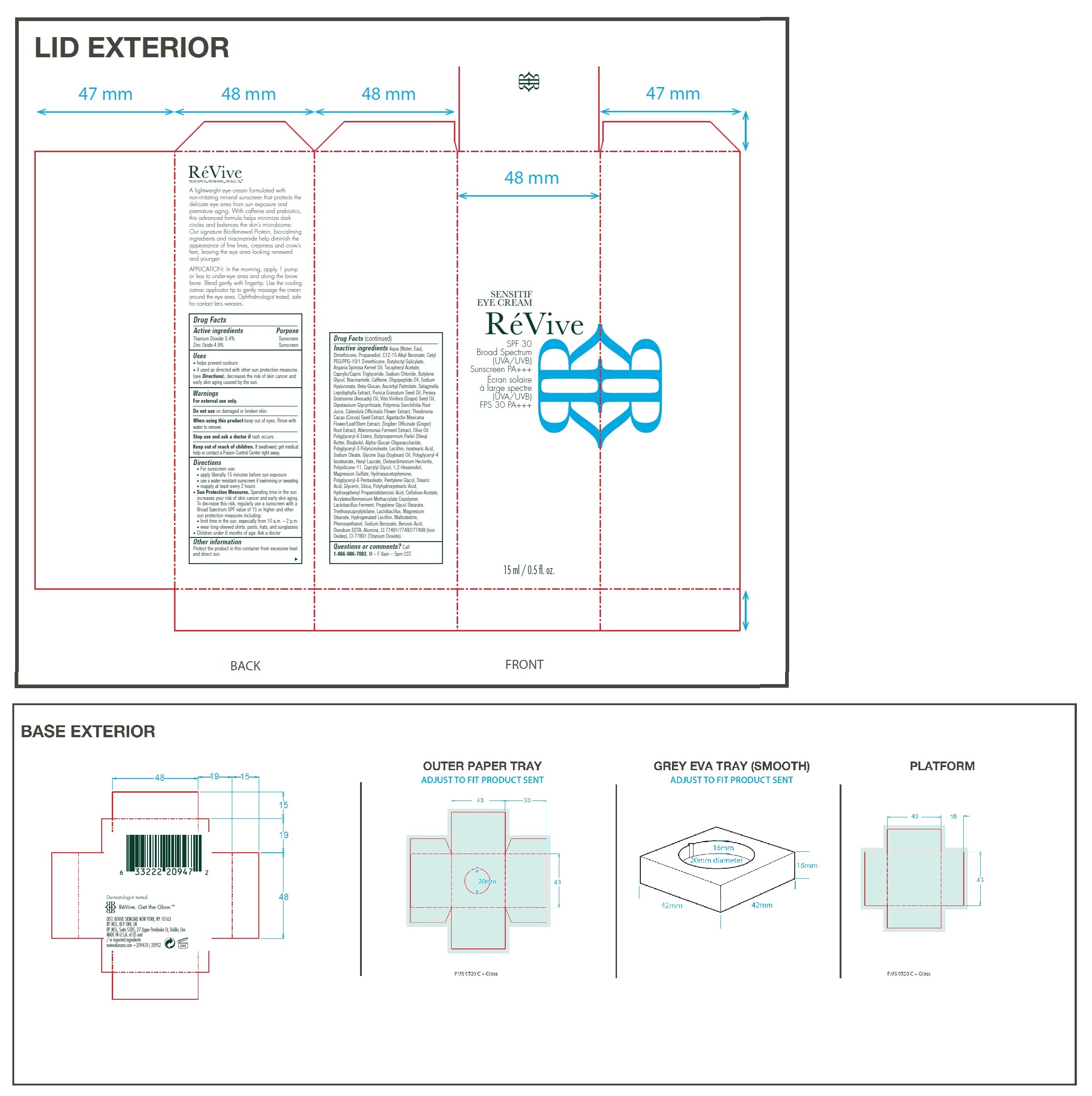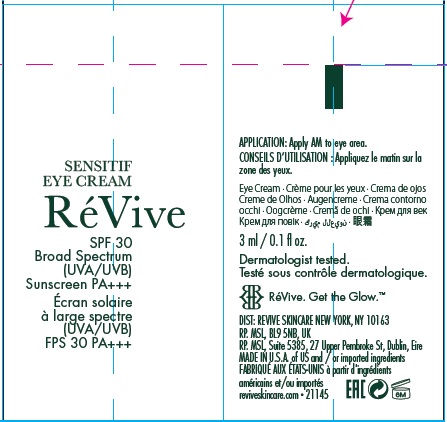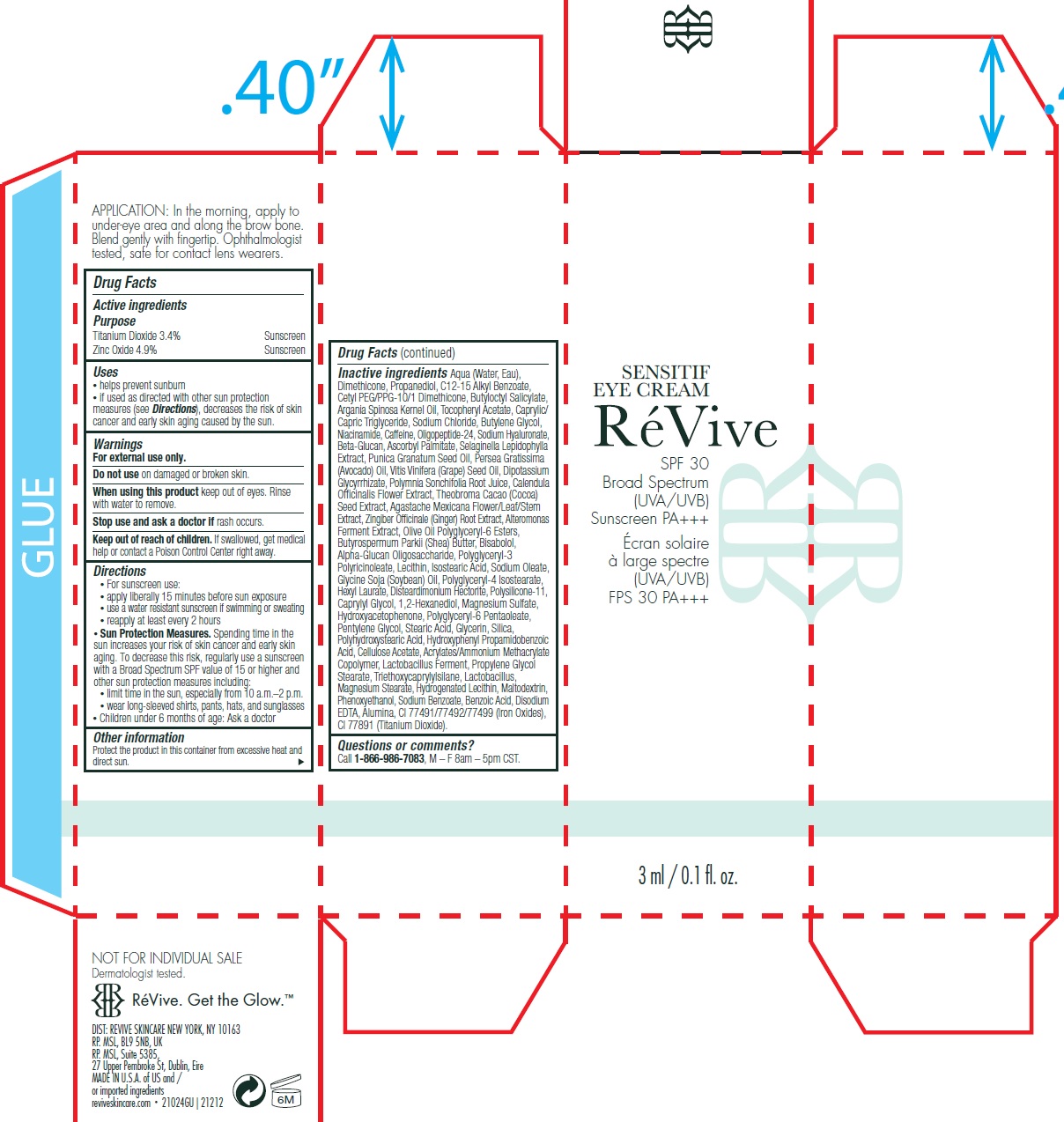 DRUG LABEL: Sensitif Eye US SPF 30 Broad Spectrum UVA UVB Sunscreen PA
NDC: 82691-144 | Form: CREAM
Manufacturer: RV Skincare LLC
Category: otc | Type: HUMAN OTC DRUG LABEL
Date: 20231106

ACTIVE INGREDIENTS: TITANIUM DIOXIDE 34 mg/1 mL; ZINC OXIDE 49 mg/1 mL
INACTIVE INGREDIENTS: WATER; DIMETHICONE; PROPANEDIOL; ALKYL (C12-15) BENZOATE; BUTYLOCTYL SALICYLATE; ARGAN OIL; .ALPHA.-TOCOPHEROL ACETATE; MEDIUM-CHAIN TRIGLYCERIDES; SODIUM CHLORIDE; BUTYLENE GLYCOL; NIACINAMIDE; CAFFEINE; HYALURONATE SODIUM; ASCORBYL PALMITATE; POMEGRANATE SEED OIL; AVOCADO OIL; GRAPE SEED OIL; GLYCYRRHIZINATE DIPOTASSIUM; CALENDULA OFFICINALIS FLOWER; COCOA; GINGER; OLIVE OIL POLYGLYCERYL-6 ESTERS; SHEA BUTTER; LEVOMENOL; ISOSTEARIC ACID; SODIUM OLEATE; SOYBEAN OIL; POLYGLYCERYL-4 ISOSTEARATE; HEXYL LAURATE; DISTEARDIMONIUM HECTORITE; DIMETHICONE/VINYL DIMETHICONE CROSSPOLYMER (SOFT PARTICLE); CAPRYLYL GLYCOL; 1,2-HEXANEDIOL; MAGNESIUM SULFATE, UNSPECIFIED FORM; HYDROXYACETOPHENONE; PENTYLENE GLYCOL; STEARIC ACID; GLYCERIN; SILICON DIOXIDE; HYDROXYPHENYL PROPAMIDOBENZOIC ACID; CELLULOSE ACETATE; PROPYLENE GLYCOL MONOSTEARATE; TRIETHOXYCAPRYLYLSILANE; MAGNESIUM STEARATE; MALTODEXTRIN; PHENOXYETHANOL; SODIUM BENZOATE; BENZOIC ACID; EDETATE DISODIUM ANHYDROUS; ALUMINUM OXIDE; FERRIC OXIDE RED; FERRIC OXIDE YELLOW; FERROSOFERRIC OXIDE

Sensitif Eye Cream - US SPF 30 Broad Spectrum (UVA/UVB) Sunscreen PA+++

Active ingredients

Titanium Dioxide 3.4%

Zinc Oxide 4.9%

Purpose

Sunscreen

Uses

• helps prevent sunburn

• if used as directed with other sun protection measures (see), decreases the risk of skin cancer and early skin aging caused by the sun. Directions

Warnings

For external use only.

Do not use

on damaged or broken skin.

When using this product

keep out of eyes. Rinse with water to remove.

Stop use and ask a doctor if

rash occurs.

Keep out of reach of children.

If swallowed, get medical help or contact a Poison Control Center right away.

Directions

• For sunscreen use: • apply liberally 15 minutes before sun exposure • use a water resistant sunscreen if swimming or sweating • reapply at least every 2 hours • Spending time in the sun increases your risk of skin cancer and early skin aging. To decrease this risk, regularly use a sunscreen with a Broad Spectrum SPF value of 15 or higher and other sun protection measures including: • limit time in the sun, especially from 10 a.m. – 2 p.m. • wear long-sleeved shirts, pants, hats, and sunglasses • Children under 6 months of age: Ask a doctor
Sun Protection Measures.

Other information

Protect the product in this container from excessive heat and direct sun.

Inactive ingredients

Aqua (Water, Eau), Dimethicone, Propanediol, C12-15 Alkyl Benzoate, Cetyl PEG/PPG-10/1 Dimethicone, Butyloctyl Salicylate, Argania Spinosa Kernel Oil, Tocopheryl Acetate, Caprylic/Capric Triglyceride, Sodium Chloride, Butylene Glycol, Niacinamide, Caffeine, Oligopeptide-24, Sodium Hyaluronate, Beta-Glucan, Ascorbyl Palmitate, Selaginella Lepidophylla Extract, Punica Granatum Seed Oil, Persea Gratissima (Avocado) Oil, Vitis Vinifera (Grape) Seed Oil, Dipotassium Glycyrrhizate, Polymnia Sonchifolia Root Juice, Calendula Officinalis Flower Extract, Theobroma Cacao (Cocoa) Seed Extract, Agastache Mexicana Flower/Leaf/Stem Extract, Zingiber Officinale (Ginger) Root Extract, Alteromonas Ferment Extract, Olive Oil Polyglyceryl-6 Esters, Butyrospermum Parkii (Shea) Butter, Bisabolol, Alpha-Glucan Oligosaccharide, Polyglyceryl-3 Polyricinoleate, Lecithin, Isostearic Acid, Sodium Oleate, Glycine Soja (Soybean) Oil, Polyglyceryl-4 Isostearate, Hexyl Laurate, Disteardimonium Hectorite, Polysilicone-11, Caprylyl Glycol, 1,2-Hexanediol, Magnesium Sulfate, Hydroxyacetophenone, Polyglyceryl-6 Pentaoleate, Pentylene Glycol, Stearic Acid, Glycerin, Silica, Polyhydroxystearic Acid, Hydroxyphenyl Propamidobenzoic Acid, Cellulose Acetate, Acrylates/Ammonium Methacrylate Copolymer, Lactobacillus Ferment, Propylene Glycol Stearate, Triethoxycaprylylsilane, Lactobacillus, Magnesium Stearate, Hydrogenated Lecithin, Maltodextrin, Phenoxyethanol, Sodium Benzoate, Benzoic Acid, Disodium EDTA, Alumina, CI 77491/77492/77499 (Iron Oxides), CI 77891 (Titanium Dioxide).

Questions or comments?

Call M – F 8am – 5pm CST. 1-866-986-7083,